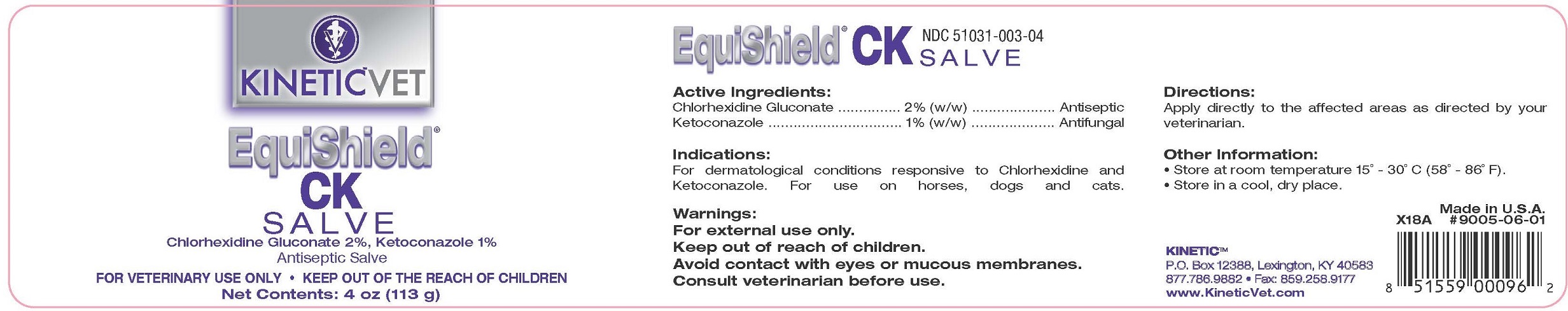 DRUG LABEL: EquiShield CK
NDC: 51031-003 | Form: SALVE
Manufacturer: Kinetic Technologies, LLC
Category: animal | Type: OTC ANIMAL DRUG LABEL
Date: 20231127

ACTIVE INGREDIENTS: CHLORHEXIDINE GLUCONATE 2 g/100 g; KETOCONAZOLE 1 g/100 g

EquiShield® CK Salve

Active Ingredients:

Chlorhexidine Gluconate ........... 2% (w/w)............ Antiseptic
Ketoconazole ........................... 1% (w/w)........... Antifungal

Indications:

For dermatological conditions responsive to Chlorhexidine and Ketoconazole. For use on horses, dogs and cats.

Warnings:

For external use only.

Keep out of reach of children.

Avoid contact with eyes or mucous membranes.

Consult veterinarian before use.

Directions:

Apply directly to the affected areas as directed by your veterinarian.

Other Information:

• Store at room temperature 15˚ - 30˚C (58˚ - 86˚F).
• Store in a cool, dry place.

NDC 51031-003-01

NDC 51031-003-04

KINETIC™

P.O. Box 12388, Lexington, KY 40583

877.786.9882 • Fax: 859.258.9177

www.KineticVet.com

Made In U.S.A.

KINETIC™VET

EquiShield® CK SALVE

Chlorhexidine Gluconate 2%, Ketoconazole 1%

Antiseptic Salve

FOR VETERINARY USE ONLY • KEEP OUT OF REACH OF CHILDREN

Net contents: 4 oz (113 g)

EquiShield CK Salve 51031-003-04.jpg